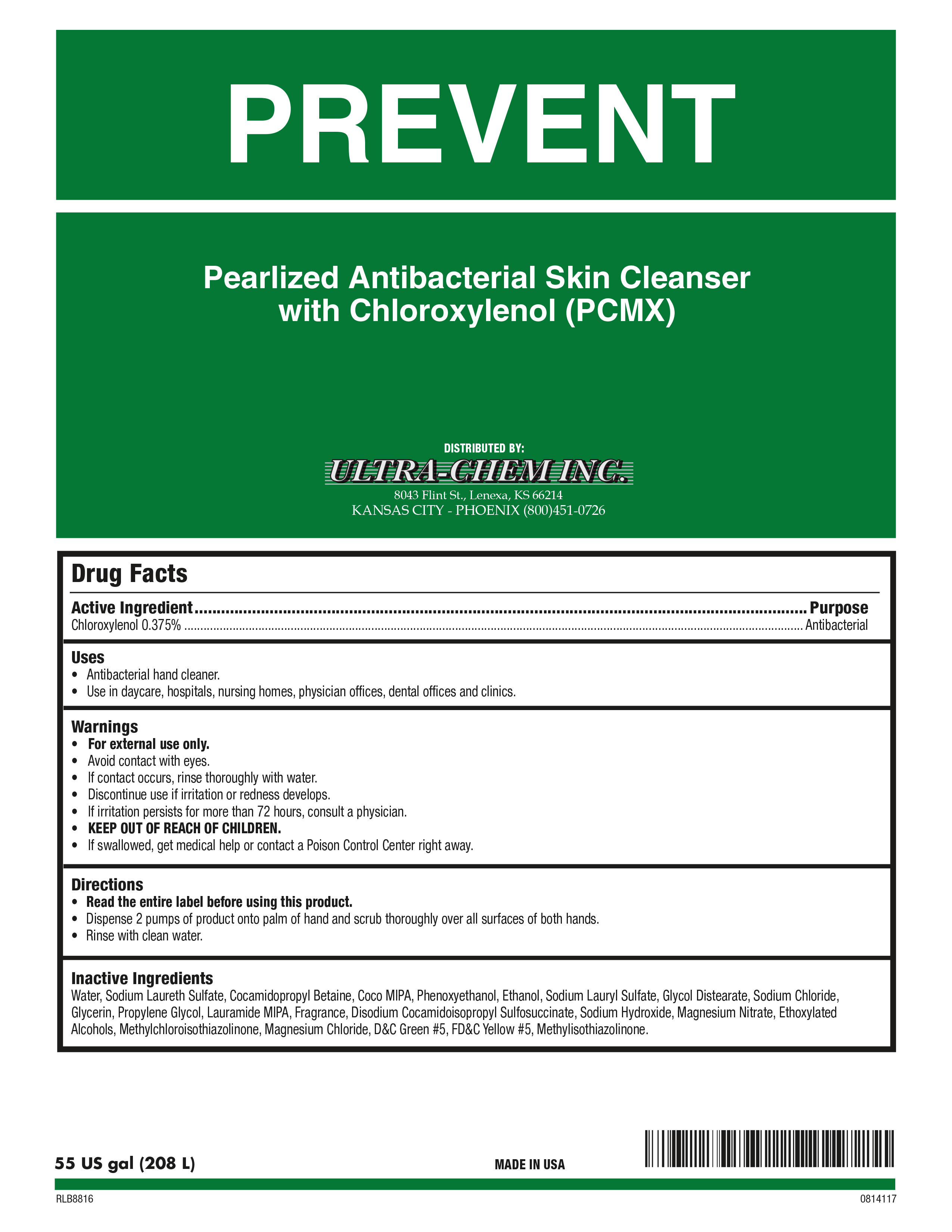 DRUG LABEL: Prevent
NDC: 66077-708 | Form: SOAP
Manufacturer: Ultra-Chem Inc.
Category: otc | Type: HUMAN OTC DRUG LABEL
Date: 20241226

ACTIVE INGREDIENTS: CHLOROXYLENOL 3.75 mg/1 mL
INACTIVE INGREDIENTS: BENZYL BENZOATE; SODIUM HYDROXIDE; METHYL ANTHRANILATE; SODIUM ALUMINIUM SILICATE; ETHYL ACETOACETATE; GLYCOL DISTEARATE; .GAMMA.-DECALACTONE; ETHYLENE OXIDE; WATER; SODIUM LAURYL SULFATE; COCO DIETHANOLAMIDE; COCAMIDOPROPYL BETAINE; PHENOXYETHANOL; PROPYLENE GLYCOL; ETHYL BUTYRATE; LAURIC DIETHANOLAMIDE; CALCIUM SILICATE; D&C GREEN NO. 5; FD&C YELLOW NO. 5; METHYLCHLOROISOTHIAZOLINONE; DIOXANE; DIMETHYL BENZYL CARBINYL ACETATE; METHYLISOTHIAZOLINONE; MAGNESIUM NITRATE; SODIUM CARBONATE; TRIBASIC CALCIUM PHOSPHATE; SODIUM FERROCYANIDE; LAURIC ISOPROPANOLAMIDE; METHYL ALCOHOL; ETHYL METHYLPHENYLGLYCIDATE; LINALOOL, (+/-)-; CHLOROACETIC ACID; DIMETHYL BENZYL CARBINYL BUTYRATE

Prevent

Prevent

Active Ingredient

Chloroxylenol 0.375%

Prevent

Uses

- Antibacterial hand cleaner.
- Use in daycare, hospitals, nursing homes, physicians offices, dental offices and clinics

Prevent

Warnings

- For external use only.
- Avoid contact with eyes.
- Children under the age of 6 should be supervised by an adult when using this product.
- Discontinue use is irritation or redness develops.
- If irritation persists for more than 72 hours, consult a physician.
- KEEP OUT OF REACH OF CHILDREN.

Prevent

Directions

- Read the entire label before using this product.
- Dispense 1-2 pumps of product onto wet palm.
- Lather and rinse hands with clean water

Prevent

Inactive Ingredients

Water, Sodium Lauryl lSulfate, Cocamide DEA, Cocamidopropyl betadine, Phenoxyethanol, Sodium Laureth Sulfate, Propylene Glycol, Fragrance, DMDM Hydantoin, Glycol Stearate, Laurimide DEA, Glycerine, Tocopheryl Acetate, D&C Green #5, FD&C Yellow #5.

Prevent

Purpose

Antibacterial

Prevent

Winning Hands Antibacterial

KEEP OUT OF REACH OF CHILDREN

Prevent

UltraChem 141